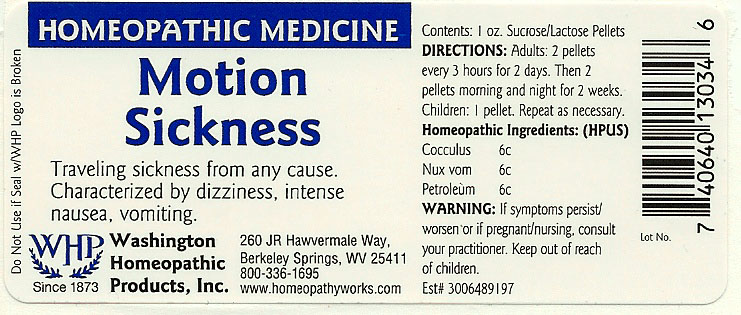 DRUG LABEL: Motion Sickness
NDC: 68428-024 | Form: PELLET
Manufacturer: Washington Homeopathic Products
Category: homeopathic | Type: HUMAN OTC DRUG LABEL
Date: 20191223

ACTIVE INGREDIENTS: ANAMIRTA COCCULUS SEED 6 [hp_C]/28 g; STRYCHNOS NUX-VOMICA SEED 6 [hp_C]/28 g; KEROSENE 6 [hp_C]/28 g
INACTIVE INGREDIENTS: SUCROSE; LACTOSE

DRUG FACTS

ACTIVE INGREDIENTS

COCCULUS 6C

NUX VOM 6C

PETROLEUM 6C

USES

To relieve the symptoms of traveling sickness from any cause. Characterized by dizziness, intense nausea, vomiting.

KEEP OUT OF REACH OF CHILDREN

Keep this and all medicines out of reach of children.

INDICATIONS

COCCULUS Motion sickness

NUX VOM Vomiting

PETROLEUM Nausea

STOP USE AND ASK DOCTOR

If symptoms persist/worsen or if pregnant/nursing, stop use and consult your practitioner.

DIRECTIONS

Adults 2 pellets every 3 hours for 2 days. Then 2 pellets morning and night for 2 weeks.

Children: 1 pellet. Repeat as necessary.

INACTIVE INGREDIENTS

Sucrose/Lactose

PRINCIPAL DISPLAY PANEL

Enter section text here